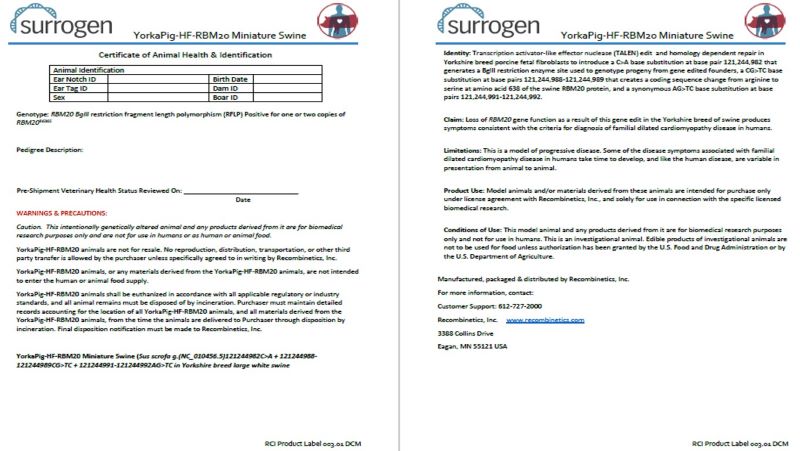 DRUG LABEL: YorkaPig-HF-RBM20 Swine
NDC: 86086-003 | Form: NOT APPLICABLE
Manufacturer: Recombinetics, Inc.
Category: other | Type: INTENTIONAL ANIMAL GENOMIC ALTERATION LABEL
Date: 20240724

ACTIVE INGREDIENTS: SUS SCROFA G.(NC_010456.5)121244982C>A + 121244988-121244989CG>TC + 121244991-121244992AG>TC ALTERATION TO EXON 9 OF RBM20 GENE IN YORKSHIRE BREED LARGE WHITE SWINE 1 [arb'U]/1 [arb'U]

YorkaPig-HF-RBM20 Swine

STATEMENT OF IDENTITY

Identity: Transcription activator-like effector nuclease (TALEN) edit and homology dependent repair in Yorkshire breed porcine fetal fibroblasts to introduce a C>A base substitution at base pair 121,244,982 that generates a BglII restriction enzyme site used to genotype progeny from gene edited founders, a CG>TC base substitution at base pairs 121,244,988-121,244,989 that creates a coding sequence change from arginine to serine at amino acid 638 of the swine RBM20 protein, and a synonymous AG>TC base substitution at base pairs 121,244,991-121,244,992.

HEALTH CLAIM

Claim: Loss of RBM20 gene function as a result of this gene edit in the Yorkshire breed of swine produces symptoms consistent with the criteria for diagnosis of familial dilated cardiomyopathy disease in humans.

CONTRAINDICATIONS

Limitations: This is a model of progressive disease. Some of the disease symptoms associated with familial dilated cardiomyopathy disease in humans take time to develop, and like the human disease, are variable in presentation from animal to animal.

INDICATIONS AND USAGE

Product Use: Model animals and/or materials derived from these animals are intended for purchase only under license agreement with Recombinetics, Inc., and solely for use in connection with the specific licensed biomedical research.

INDICATIONS AND USAGE

Conditions of Use: This model animal and any products derived from it are for biomedical research purposes only and not for use in humans. This is an investigational animal. Edible products of investigational animals are not to be used for food unless authorization has been granted by the U.S. Food and Drug Administration or by the U.S. Department of Agriculture.

WARNINGS & PRECAUTIONS:
Caution. This intentionally genetically altered animal and any products derived from it are for biomedical
research purposes only and are not for use in humans or as human or animal food.
YorkaPig-HF-RBM20 animals are not for resale. No reproduction, distribution, transportation, or other third
party transfer is allowed by the purchaser unless specifically agreed to in writing by Recombinetics, Inc.
YorkaPig-HF-RBM20 animals, or any materials derived from the YorkaPig-HF-RBM20 animals, are not intended
to enter the human or animal food supply.
YorkaPig-HF-RBM20 animals shall be euthanized in accordance with all applicable regulatory or industry
standards, and all animal remains must be disposed of by incineration. Purchaser must maintain detailed
records accounting for the location of all YorkaPig-HF-RBM20 animals, and all materials derived from the
YorkaPig-HF-RBM20 animals, from the time the animals are delivered to Purchaser through disposition by
incineration. Final disposition notification must be made to Recombinetics, Inc.